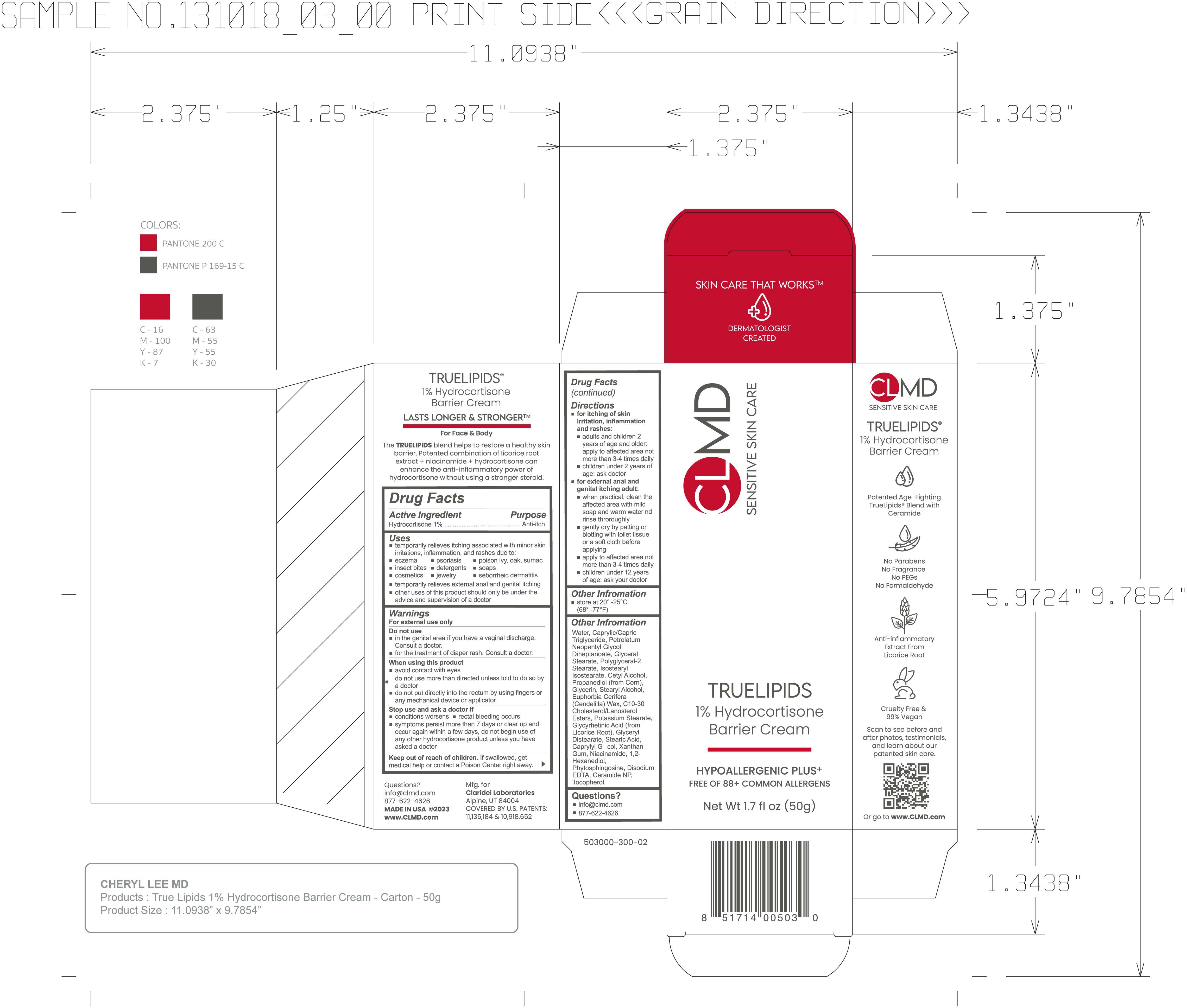 DRUG LABEL: TrueLipids 1% Hydrocortisone Barrier Cream
NDC: 61387-252 | Form: CREAM
Manufacturer: Claridei Laboratories
Category: otc | Type: HUMAN OTC DRUG LABEL
Date: 20251215

ACTIVE INGREDIENTS: HYDROCORTISONE 1 g/100 g
INACTIVE INGREDIENTS: MEDIUM-CHAIN TRIGLYCERIDES; TOCOPHEROL; POLYGLYCERYL-2 STEARATE; CANDELILLA WAX; POTASSIUM STEARATE; ENOXOLONE; STEARIC ACID; GLYCERYL MONOSTEARATE; C10-30 CHOLESTEROL/LANOSTEROL ESTERS; CAPRYLYL GLYCOL; NIACINAMIDE; PHYTOSPHINGOSINE; EDETATE DISODIUM ANHYDROUS; PETROLATUM; GLYCERIN; GLYCERYL DISTEARATE; XANTHAN GUM; 1,2-HEXANEDIOL; CERAMIDE NP; ISOSTEARYL ISOSTEARATE; WATER; NEOPENTYL GLYCOL DIHEPTANOATE; STEARYL ALCOHOL; CETYL ALCOHOL; PROPANEDIOL

TrueLipids 1% Hydrocortisone Barrier Cream

Active Ingredient.........Purpose

Hydrocortisone 1% .....Anti-itch

Uses

- temporarily relieves itching associated with minor skin irritations, inflammation, and rashes due to:
- eczema
- psoriasis
- poison ivy, oak, sumac
- insect bites
- detergents
- soaps
- cosmetics
- jewelry
- seborrheic dermatitis
- temporarily relieves external anal and genital itching
- other uses of this product should only be under the advice and supervision of a doctor

Keep out of reach of children.

If swallowed, get medical help or contact a Poison Control Center right away.

Stop use and ask a doctor if

- condition worsens
- rectal bleeding occurs
- symptoms persist more than 7 days or clear up and occur again within a few days. do not begin use of any other hydrocortisone product unless you have asked a doctor

Warnings

For external use only

Do not use

- in the genital area if you have a vaginal discharge. consult a doctor
- for the treatment of diaper rash. consult a doctor

when using this product

avoid contact with eyes

do not use more than directed unless told to do so by a doctor

do not put directly into rectim by using fingers or any mechanical device or applicator

Directions

- for itching of skin irritation, inflammation and rashes:
  - adults and children 2 years of age and older: apply to affected area not more than 3-4 times daily
  - children under 2 years of age: ask a doctor
  - for external anal and genital itching adult:
    - when practical clean the affected area with mild soap and water and rinse thoroughly
  - gently dry by patting or blotting with toilet tissueor a soft cloth before applying

Inactive ingredients

Water, Caprylic/capric Triglyceride, Petrolatum, Neopentyl Glycol Diheptanoate, Glyceryl Stearate, Polyglyceryl-2 Stearate, Isostearyl Isostearate, Cetyl Allcohol, Propanediol (from Corn) , Glycerin, Stearyl Alcohol, Euphorbia Cerifera (Candelilla Wax), C10-30 Cholesterol/Lanosterol Esters, Potassium Stearate, Glycyrrhetinic Acid(from Licorice root), Glyceryl Distearate, Stearic Acid, Caprylyl Glycol, Xanthan Gum, Niacinamide, 1,2-Hexanediol, Phytospingosine, Disodium EDTA, Ceramide NP, Tocopherol

Other information

store at 20°-25ºC (68º-77ºF)

PACKAGE LABEL

CLMD

Sensitive Skin Care

True Lipids

1% Hydrocortisone Barrier Cream

Net Wt 1.7 fl oz (50g)